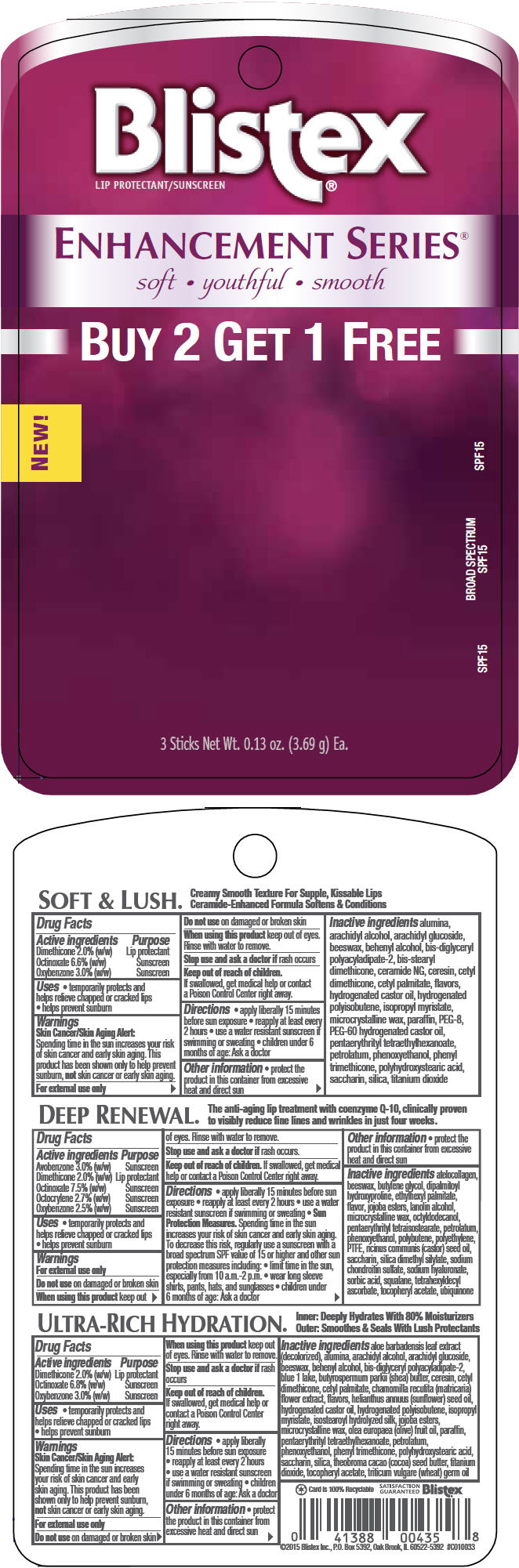 DRUG LABEL: Blistex Enhancement Series (Soft and Lush, Deep Renewal and Ultra-Rich Hydration)
NDC: 10157-9867 | Form: KIT | Route: TOPICAL
Manufacturer: Blistex Inc.
Category: otc | Type: HUMAN OTC DRUG LABEL
Date: 20150828

ACTIVE INGREDIENTS: Dimethicone 2 g/100 g; Octinoxate 7.5 g/100 g; Oxybenzone 2.5 g/100 g; Dimethicone 2 g/100 g; Octinoxate 7.5 g/100 g; Oxybenzone 2.5 g/100 g; Avobenzone 3 g/100 g; Octocrylene 2.7 g/100 g; Dimethicone 2 g/100 g; Octinoxate 6.8 g/100 g; Oxybenzone 3 g/100 g
INACTIVE INGREDIENTS: PENTAERYTHRITYL TETRAETHYLHEXANOATE; HYDROGENATED POLYBUTENE (1300 MW); PETROLATUM; MICROCRYSTALLINE WAX; PARAFFIN; PHENYL TRIMETHICONE; HYDROGENATED CASTOR OIL; ISOPROPYL MYRISTATE; TITANIUM DIOXIDE; ALUMINUM OXIDE; SILICON DIOXIDE; YELLOW WAX; CERESIN; CETYL PALMITATE; ARACHIDYL ALCOHOL; DOCOSANOL; ARACHIDYL GLUCOSIDE; CERAMIDE 2; PHENOXYETHANOL; SACCHARIN; POLYHYDROXYSTEARIC ACID (2300 MW); PEG-60 HYDROGENATED CASTOR OIL; POLYETHYLENE GLYCOL 400; CETYL DIMETHICONE 150; STEARYL DIMETHICONE (400 MPA.S AT 50C); YELLOW WAX; BUTYLENE GLYCOL; DIPALMITOYL HYDROXYPROLINE; ETHYLHEXYL PALMITATE; LANOLIN ALCOHOLS; MICROCRYSTALLINE WAX; OCTYLDODECANOL; PENTAERYTHRITYL TETRAISOSTEARATE; PETROLATUM; PHENOXYETHANOL; HIGH DENSITY POLYETHYLENE; POLYTETRAFLUOROETHYLENE; CASTOR OIL; SACCHARIN; SILICA DIMETHYL SILYLATE; HYALURONATE SODIUM; SORBIC ACID; SQUALANE; TETRAHEXYLDECYL ASCORBATE; POLYBUTENE (1400 MW); MARINE COLLAGEN, SOLUBLE; CHONDROITIN SULFATE SODIUM (SHARK); UBIDECARENONE; SIMMONDSIA CHINENSIS SEED WAX; .ALPHA.-TOCOPHEROL ACETATE; YELLOW WAX; PENTAERYTHRITYL TETRAETHYLHEXANOATE; PETROLATUM; PARAFFIN; HYDROGENATED CASTOR OIL; MICROCRYSTALLINE WAX; ISOPROPYL MYRISTATE; TITANIUM DIOXIDE; SHEA BUTTER; ALUMINUM OXIDE; SILICON DIOXIDE; CETYL PALMITATE; ARACHIDYL ALCOHOL; DOCOSANOL; ARACHIDYL GLUCOSIDE; OLIVE OIL; ALOE VERA LEAF; .ALPHA.-TOCOPHEROL ACETATE; WHEAT GERM OIL; PHENYL TRIMETHICONE; SUNFLOWER OIL; CHAMOMILE; CERESIN; COCOA BUTTER; SACCHARIN; FD&C BLUE NO. 1; PHENOXYETHANOL

Blistex® Enhancement Series® (Soft and Lush®, Deep Renewal® and Ultra-Rich Hydration®)

SOFT & LUSH®

Drug Facts

ACTIVE INGREDIENT

Active ingredients | Purpose
Dimethicone 2.0% (w/w) | Lip protectant
Octinoxate 6.6% (w/w) | Sunscreen
Oxybenzone 3.0% (w/w) | Sunscreen

Uses

- temporarily protects and helps relieve chapped or cracked lips
- helps prevent sunburn

Warnings

Skin Cancer/Skin Aging Alert

Spending time in the sun increases your risk of skin cancer and early skin aging. This product has been shown only to help prevent sunburn, not skin cancer or early skin aging.

For external use only

Do not use on damaged or broken skin

When using this product keep out of eyes. Rinse with water to remove.

Stop use and ask a doctor if rash occurs

Keep out of reach of children. If swallowed, get medical help or contact a Poison Control Center right away.

Directions

- apply liberally 15 minutes before sun exposure
- reapply at least every 2 hours
- use a water resistant sunscreen if swimming or sweating
- children under 6 months of age: Ask a doctor

Other information

- protect the product in this container from excessive heat and direct sun

Inactive ingredients

alumina, arachidyl alcohol, arachidyl glucoside, beeswax, behenyl alcohol, bis-diglyceryl polyacyladipate-2, bis-stearyl dimethicone, ceramide NG, ceresin, cetyl dimethicone, cetyl palmitate, flavors, hydrogenated castor oil, hydrogenated polyisobutene, isopropyl myristate, microcrystalline wax, paraffin, PEG-8, PEG-60 hydrogenated castor oil, pentaerythrityl tetraethylhexanoate, petrolatum, phenoxyethanol, phenyl trimethicone, polyhydroxystearic acid, saccharin, silica, titanium dioxide

DEEP RENEWAL®

Drug Facts

ACTIVE INGREDIENT

Active ingredients | Purpose
Avobenzone 3.0% (w/w) | Sunscreen
Dimethicone 2.0% (w/w) | Lip protectant
Octinoxate 7.5% (w/w) | Sunscreen
Octocrylene 2.7% (w/w) | Sunscreen
Oxybenzone 2.5% (w/w) | Sunscreen

Uses

- temporarily protects and helps relieve chapped or cracked lips
- helps prevent sunburn

Warnings

For external use only

Do not use on damaged or broken skin

When using this product keep out of eyes. Rinse with water to remove.

Stop use and ask a doctor if rash occurs.

Keep out of reach of children. If swallowed, get medical help or contact a Poison Control Center right away.

Directions

- apply liberally 15 minutes before sun exposure
- reapply at least every 2 hours
- use a water resistant sunscreen if swimming or sweating
- Sun Protection Measures. Spending time in the sun increases your risk of skin cancer and early skin aging. To decrease this risk, regularly use a sunscreen with a broad spectrum SPF value of 15 or higher and other sun protection measures including:
  - limit time in the sun, especially from 10 a.m.-2 p.m.
  - wear long sleeve shirts, pants, hats, and sunglasses
- children under 6 months of age: Ask a doctor

Other information

- protect the product in this container from excessive heat and direct sun

Inactive ingredients

atelocollagen, beeswax, butylene glycol, dipalmitoyl hydroxyproline, ethylhexyl palmitate, flavor, jojoba esters, lanolin alcohol, microcrystalline wax, octyldodecanol, pentaerythrityl tetraisostearate, petrolatum, phenoxyethanol, polybutene, polyethylene, PTFE, ricinus communis (castor) seed oil, saccharin, silica dimethyl silylate, sodium chondroitin sulfate, sodium hyaluronate, sorbic acid, squalane, tetrahexyldecyl ascorbate, tocopheryl acetate, ubiquinone

ULTRA-RICH HYDRATION®

Drug Facts

ACTIVE INGREDIENT

Active ingredients | Purpose
Dimethicone 2.0% (w/w) | Lip protectant
Octinoxate 6.8% (w/w) | Sunscreen
Oxybenzone 3.0% (w/w) | Sunscreen

Uses

- temporarily protects and helps relieve chapped or cracked lips
- helps prevent sunburn

Warnings

Skin Cancer/Skin Aging Alert

Spending time in the sun increases your risk of skin cancer and early skin aging. This product has been shown only to help prevent sunburn, not skin cancer or early skin aging.

For external use only

Do not use on damaged or broken skin

When using this product keep out of eyes. Rinse with water to remove.

Stop use and ask a doctor if rash occurs

Keep out of reach of children. If swallowed, get medical help or contact a Poison Control Center right away.

Directions

- apply liberally 15 minutes before sun exposure
- reapply at least every 2 hours
- use a water resistant sunscreen if swimming or sweating
- children under 6 months of age: Ask a doctor

Other information

- protect the product in this container from excessive heat and direct sun

Inactive ingredients

aloe barbadensis leaf extract (decolorized), alumina, arachidyl alcohol, arachidyl glucoside, beeswax, behenyl alcohol, bis-diglyceryl polyacyladipate-2, blue 1 lake, butyrospermum parkii (shea) butter, ceresin, cetyl dimethicone, cetyl palmitate, chamomilla recutita (matricaria) flower extract, flavors, helianthus annuus (sunflower) seed oil, hydrogenated castor oil, hydrogenated polyisobutene, isopropyl myristate, isostearoyl hydrolyzed silk, jojoba esters, microcrystalline wax, olea europaea (olive) fruit oil, paraffin, pentaerythrityl tetraethylhexanoate, petrolatum, phenoxyethanol, phenyl trimethicone, polyhydroxystearic acid, saccharin, silica, theobroma cacao (cocoa) seed butter, titanium dioxide, tocopheryl acetate, triticum vulgare (wheat) germ oil

PRINCIPAL DISPLAY PANEL - Kit Blister Pack

Blistex®
LIP PROTECTANT/SUNSCREEN

ENHANCEMENT SERIES®

soft • youthful • smooth

BUY 2 GET 1 FREE

NEW!

BROAD SPECTRUM
SPF15
SPF15
SPF15

3 Sticks Net Wt. 0.13 oz. (3.69 g) Ea.